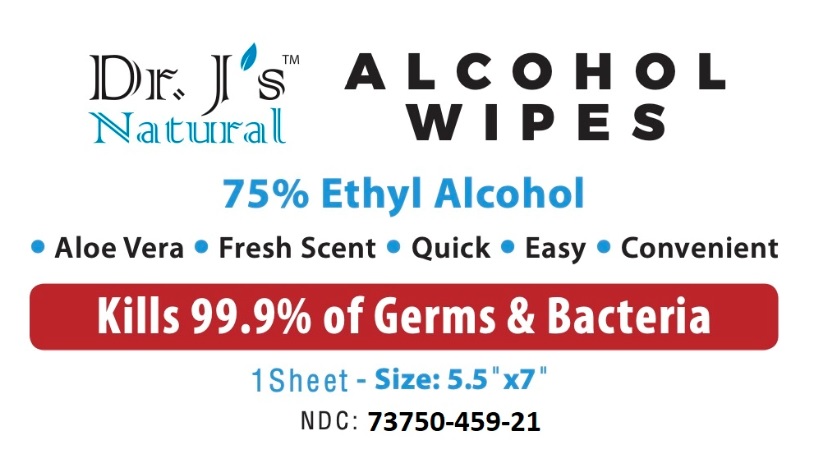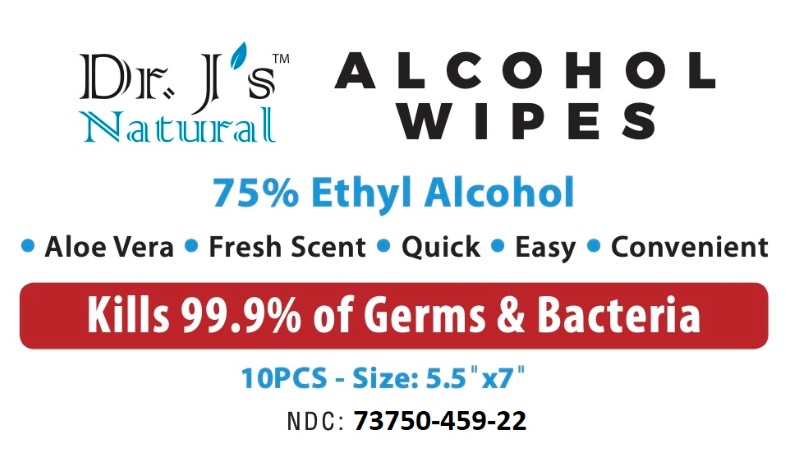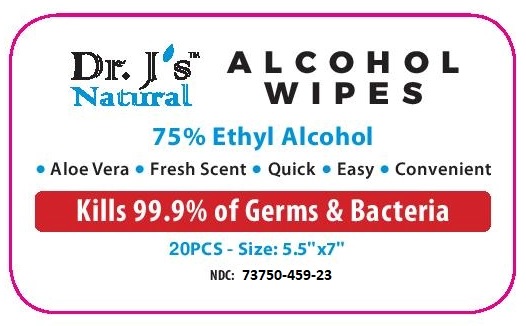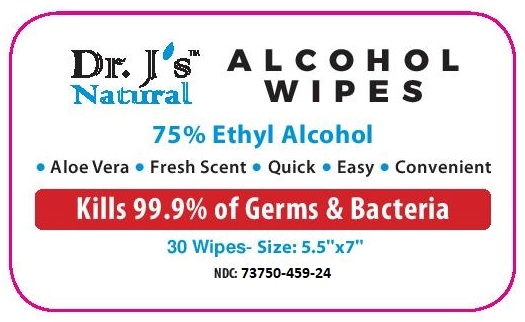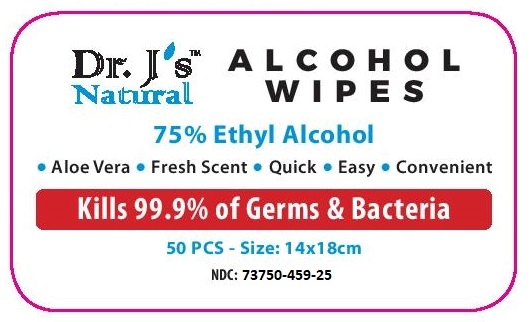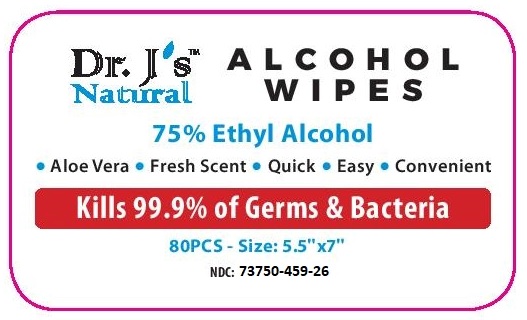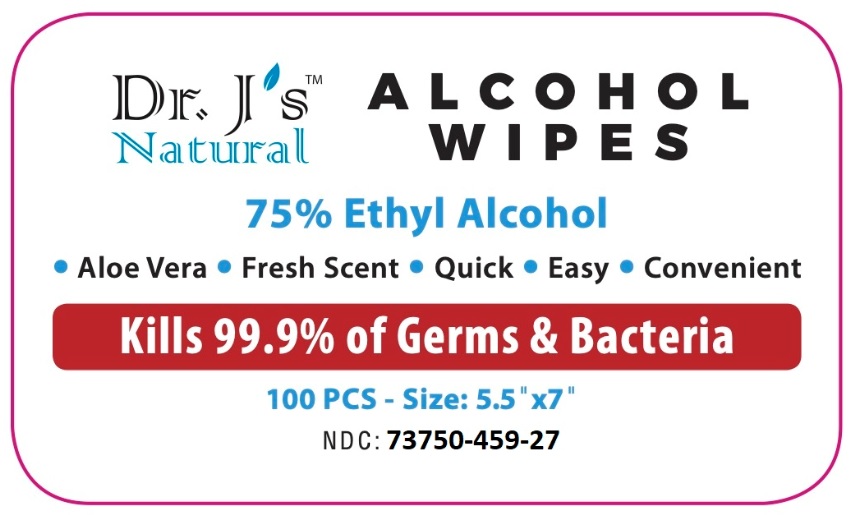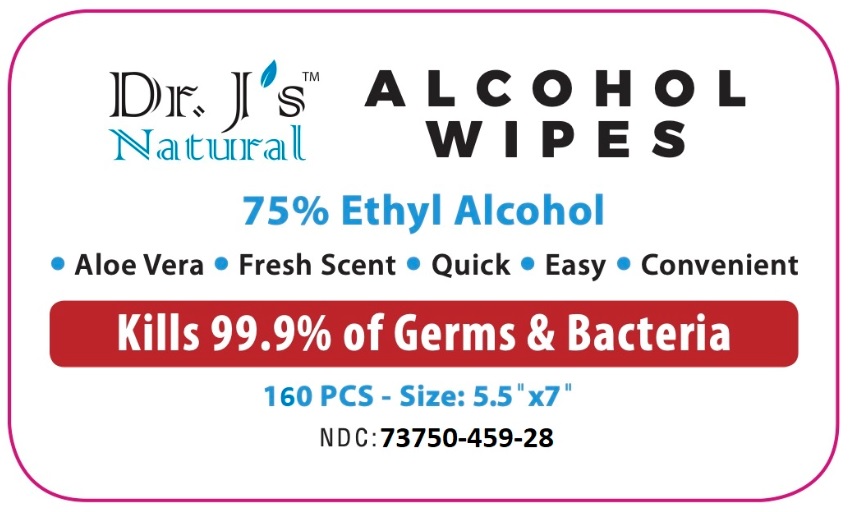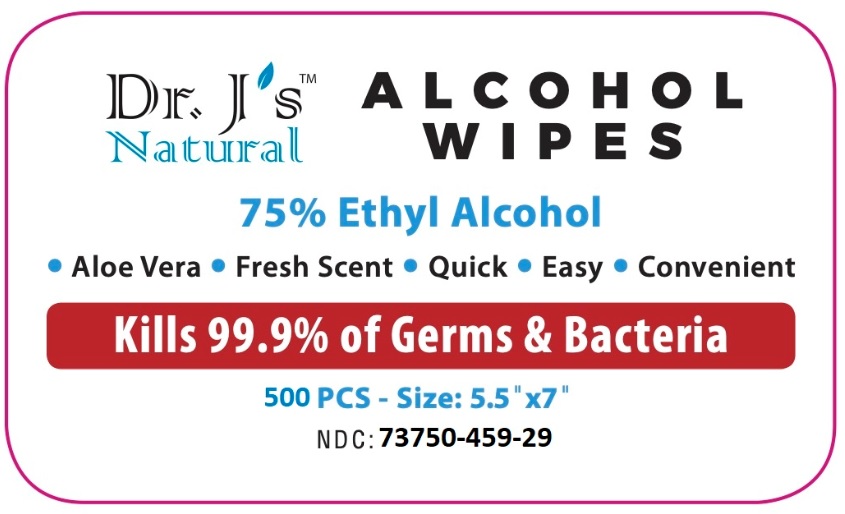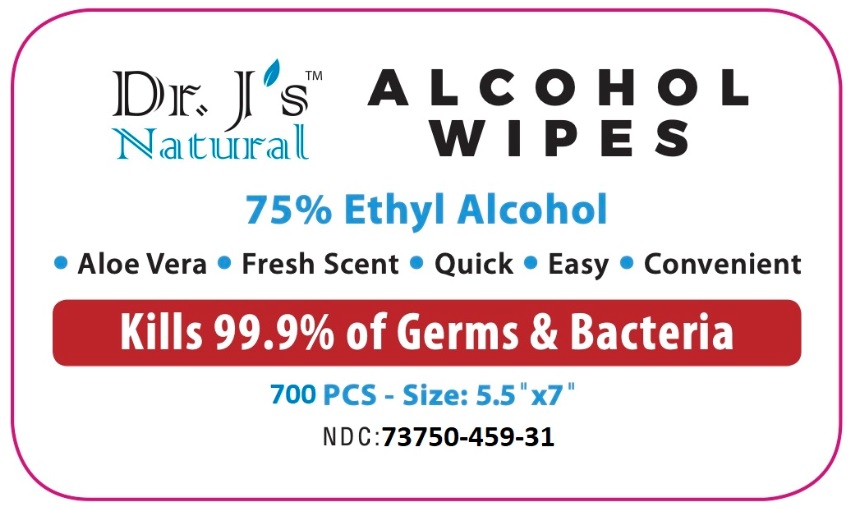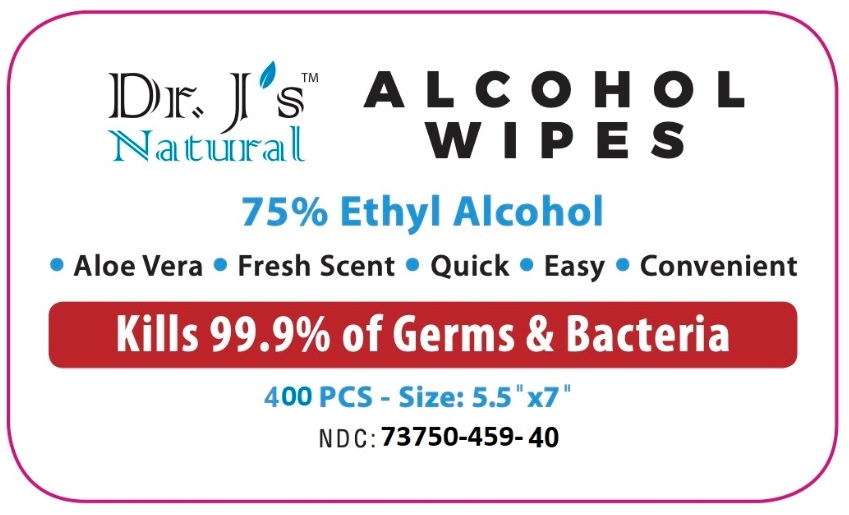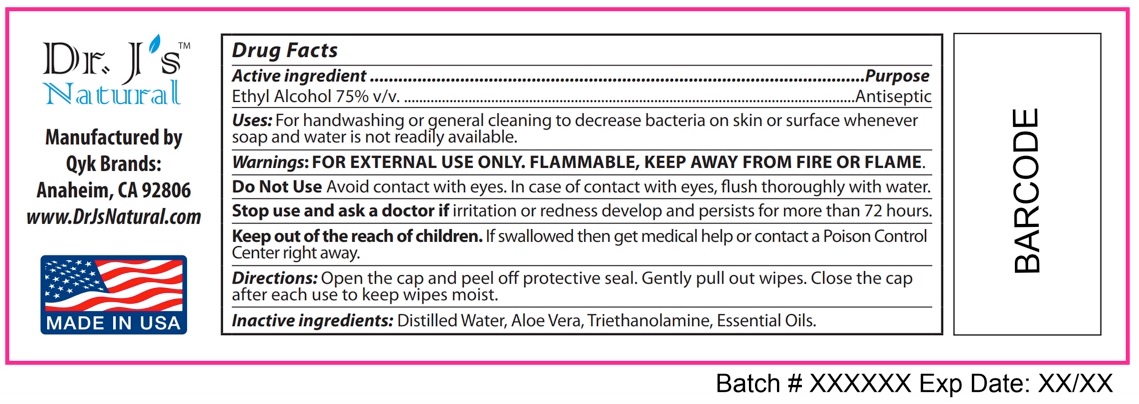 DRUG LABEL: Dr Js Natural 75% Alcohol Wipes
NDC: 73750-459 | Form: CLOTH
Manufacturer: Qyk Brands LLC
Category: otc | Type: HUMAN OTC DRUG LABEL
Date: 20200929

ACTIVE INGREDIENTS: ALCOHOL 75 mL/100 mL
INACTIVE INGREDIENTS: WATER; TRIETHANOLAMINE BENZOATE; LEMON OIL; ALOE VERA LEAF

Dr. J's Natural ALCOHOL WIPES

Active ingredient

Ethyl Alcohol 75% v/v

Purpose

Antiseptic

INDICATIONS AND USAGE

Uses: For handwashing or general cleaning to decrease bacteria on skin or surface whenever soap and water is not readily available.

WARNINGS

Warnings: FOR EXTERNAL USE ONLY. FLAMMABLE, KEEP AWAY FROM FIRE OR FLAME.

Do Not Use Avoid contact with eyes. In case of contact with eyes, flush thoroughly with water,

Stop use and ask a doctor if irritation or redness develop and persists for more than 72 hours.

KEEP OUT OF REACH OF CHILDREN

Keep out of the reach of children. If swallowed then get medical help or contact a Poison Control Center right away.

DOSAGE AND ADMINISTRATION

Directions: Open the cap and peel off protective seal. Gently pull out wipes. Close the cap after each use to keep wipes moist.

INACTIVE INGREDIENT

Inactive ingredients: Distilled Water, Aloe Vera, Triethanolamine, Essential Oils.